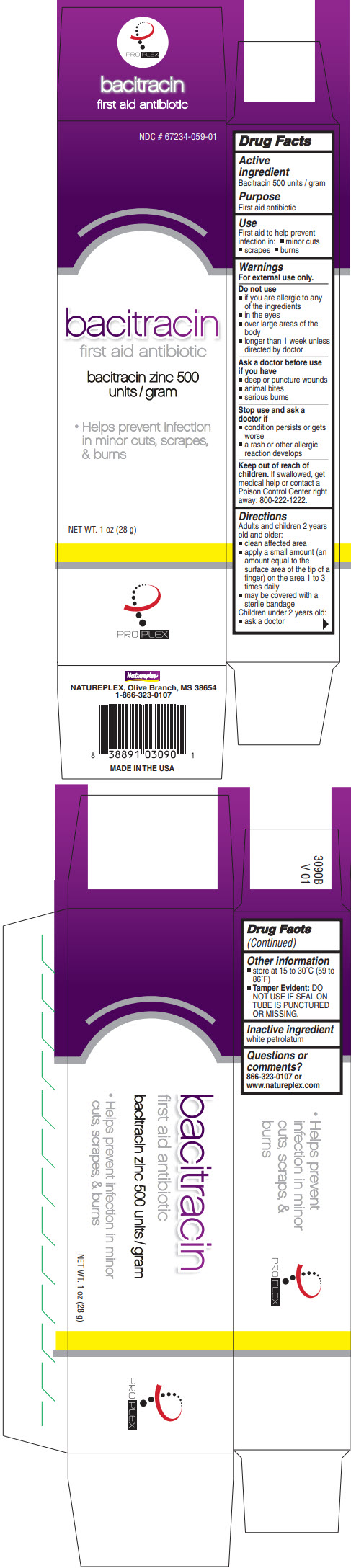 DRUG LABEL: PROPLEX BACITRACIN
NDC: 67234-059 | Form: CREAM
Manufacturer: Natureplex LLC
Category: otc | Type: HUMAN OTC DRUG LABEL
Date: 20210112

ACTIVE INGREDIENTS: BACITRACIN 500 U/1 g
INACTIVE INGREDIENTS: PETROLATUM

PROPLEX BACITRACIN

Drug Facts

Active ingredient

Bacitracin 500 units / gram

Purpose

First aid antibiotic

Use

First aid to help prevent infection in:

- minor cuts
- scrapes
- burns

Warnings

For external use only.

Do not use

- if you are allergic to any of the ingredients
- in the eyes
- over large areas of the body
- longer than 1 week unless directed by doctor

Ask a doctor before use if you have

- deep or puncture wounds
- animal bites
- serious burns

Stop use and ask a doctor if

- condition persists or gets worse
- a rash or other allergic reaction develops

Keep out of reach of children. If swallowed, get medical help or contact a Poison Control Center right away: 800-222-1222.

Directions

Adults and children 2 years old and older:

- clean affected area
- apply a small amount (an amount equal to the surface area of the tip of a finger) on the area 1 to 3 times daily
- may be covered with a sterile bandage

Children under 2 years old:

- ask a doctor

Other information

- store at 15 to 30°C (59 to 86°F)
- Tamper Evident: DO NOT USE IF SEAL ON TUBE IS PUNCTURED OR MISSING.

Inactive ingredient

white petrolatum

Questions or comments?

866-323-0107 or www.natureplex.com

PRINCIPAL DISPLAY PANEL - 28 g Tube Carton

NDC # 67234-059-01

bacitracin
first aid antibiotic

bacitracin zinc 500
units / gram

- Helps prevent infection
  in minor cuts, scrapes,
  & burns

NET WT. 1 oz (28 g)

PRO PLEX